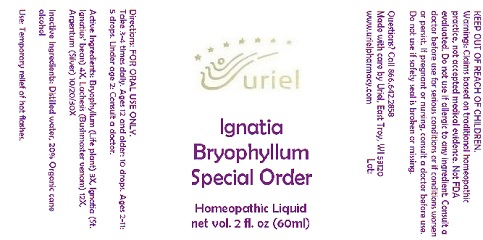 DRUG LABEL: Ignatia Bryophyllum
NDC: 48951-8306 | Form: LIQUID
Manufacturer: Uriel Pharmacy Inc.
Category: homeopathic | Type: HUMAN OTC DRUG LABEL
Date: 20180426

ACTIVE INGREDIENTS: STRYCHNOS IGNATII SEED 4 [hp_X]/1 mL; LACHESIS MUTA VENOM 12 [hp_X]/1 mL; SILVER 10 [hp_X]/1 mL; KALANCHOE DAIGREMONTIANA LEAF 3 [hp_X]/1 mL
INACTIVE INGREDIENTS: WATER; ALCOHOL

Ignatia Bryophyllum Special Order

INDICATIONS AND USAGE

Directions: FOR ORAL USE ONLY.

DOSAGE AND ADMINISTRATION

Take 3-4 times daily. Ages 12 and older: 10 drops. Ages 2-11: 5 drops. Under age 2: Consult a doctor.

ACTIVE INGREDIENT

Active Ingredients: Bryophyllum (Life plant) 3X, Ignatia (St. Ignatius’ bean) 4X, Lachesis (Bushmaster venom) 12X, Argentum (Silver) 10/20/30X

Inactive Ingredients: Distilled water, 20% Organic cane alcohol

PURPOSE

Use: Temporary relief of hot flashes.

KEEP OUT OF REACH OF CHILDREN.

WARNINGS

Warnings: Claims based on traditional homeopathic practice, not accepted medical evidence. Not FDA evaluated. Do not use if allergic to any ingredient. Consult a doctor before use for serious conditions or if conditions worsen or persist. If pregnant or nursing, consult a doctor before use. Do not use if safety seal is broken or missing.

Questions? Call 866.642.2858
Made with care by Uriel, East Troy, WI 53120
www.urielpharmacy.com